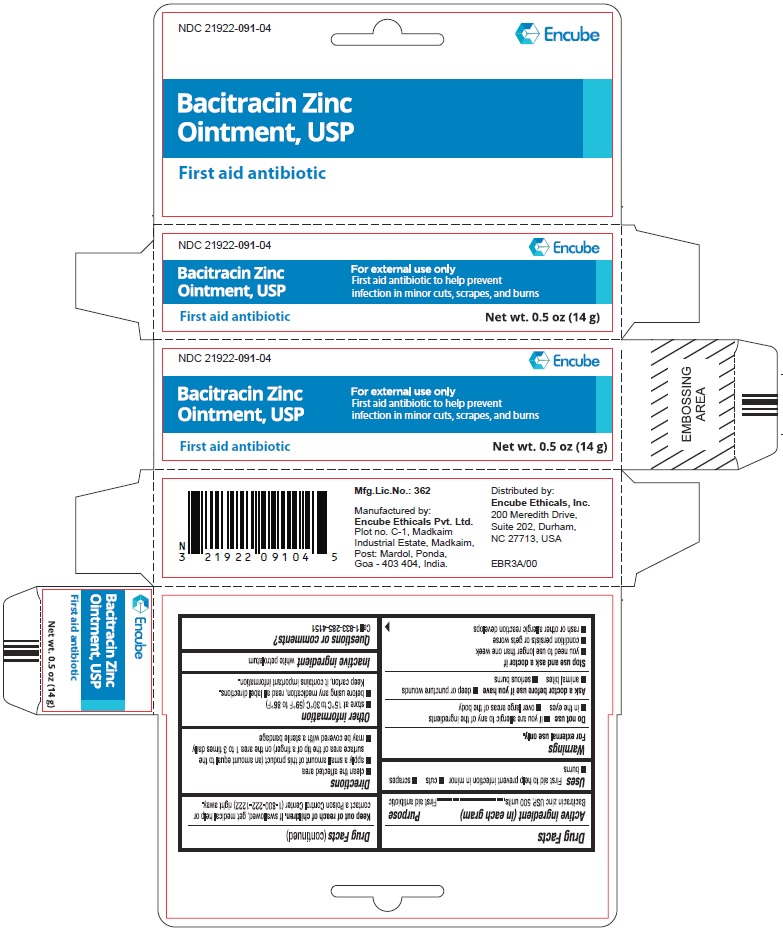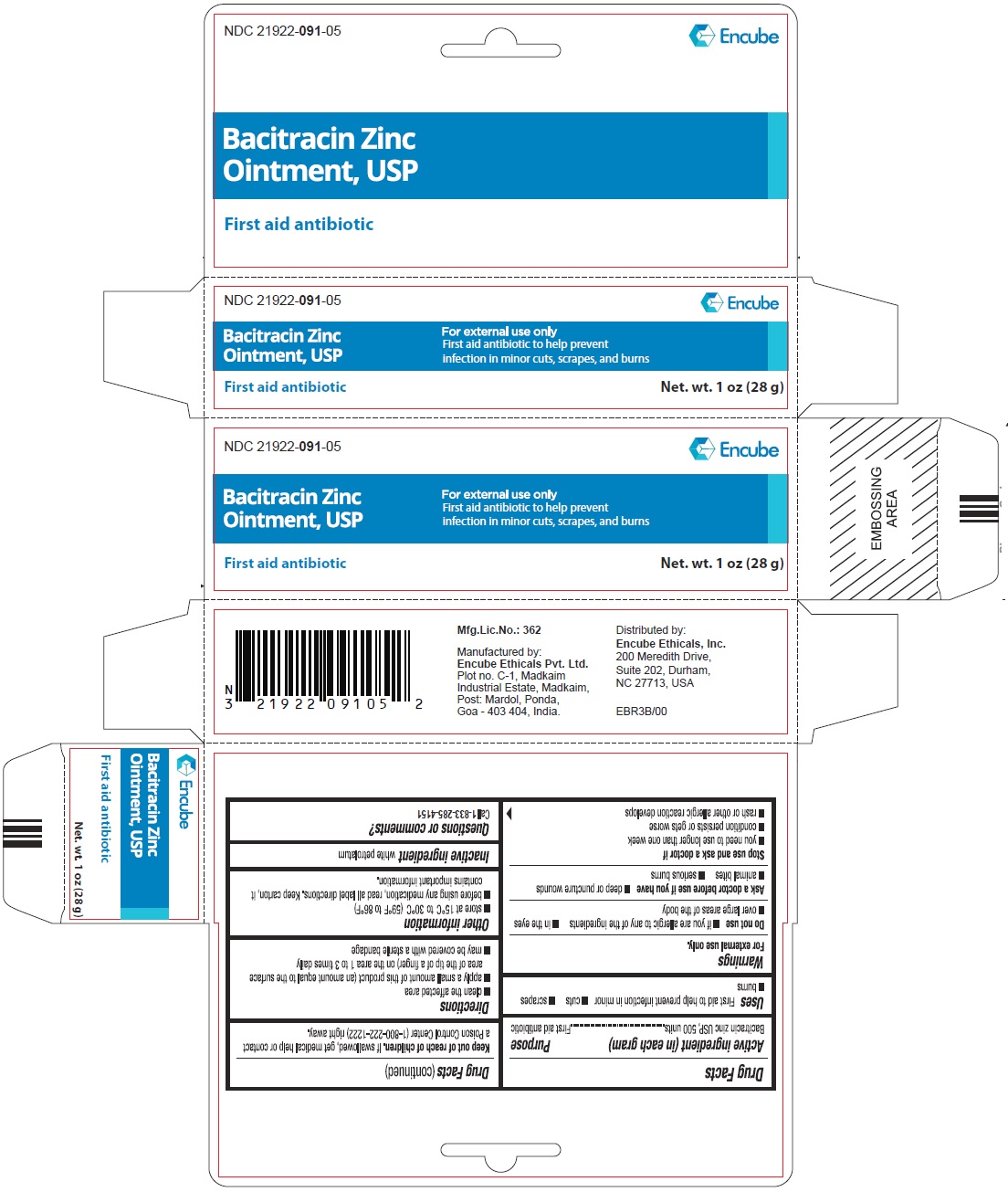 DRUG LABEL: BACITRACIN ZINC
NDC: 21922-091 | Form: OINTMENT
Manufacturer: Encube Ethicals, Inc.
Category: otc | Type: HUMAN OTC DRUG LABEL
Date: 20250904

ACTIVE INGREDIENTS: BACITRACIN ZINC 500 [USP'U]/1 g
INACTIVE INGREDIENTS: WHITE PETROLATUM

BACITRACIN ZINC OINTMENT, USP
First aid antibiotic

ACTIVE INGREDIENT(S)

(in each gram)
Bacitracin zinc, USP 500 units ............. First aid antibiotic

PURPOSE

First aid antibiotic

USE(S)

First Aid to help prevent infection in minor

- cuts
- scrapes
- burns

WARNINGS

For External Use Only.

DO NOT USE

- if you are allergic to any of the ingredients
- in the eyes
- over large areas of the body

ASK A DOCTOR BEFORE USE IF YOU HAVE

- deep or puncture wounds
- animal bites
- serious burns

STOP USE AND ASK DOCTOR IF

- you need to use longer than one week
- condition persist or gets worse
- rash or other allergic reaction develops

KEEP OUT OF REACH OF CHILDREN

If swallowed, get medical help or contact a Poison Control Center (1-800-222-1222) right away.

DIRECTIONS

- clean the affected area
- apply a small amount of this product (an amount equal to the surface area of the tip of a finger) on the area 1 to 3 times daily
- may be covered with a sterile bandage

OTHER INFORMATION

- store at 15^0C to 30^0C (59^0F to 86^0F)
- before using any medication, read all label directions. Keep carton, it contains important information.

INACTIVE INGREDIENTS

white petrolatum

QUESTIONS OR COMMENTS?

Call 1-833-285-4151

Mfg. Lic. No.: 362

Manufactured by:
Encube Ethicals Pvt. Ltd.
Plot no. C-1, Madkaim
Industrial Estate, Madkaim,
Post: Mardol, Ponda,
Goa - 403 404, India.

Distributed by:
Encube Ethicals, Inc.
200 Meredith Drive,
Suite 202, Durham,
NC 27713, USA

PRINCIPAL DISPLAY PANEL

BACITRACIN ZINC OINTMENT, USP

First aid antibiotic

NET WT. 0.5 OZ (14 g)

BACITRACIN ZINC OINTMENT, USP

First aid antibiotic

NET WT. 1 OZ (28 g)